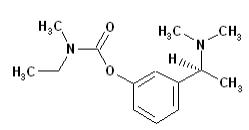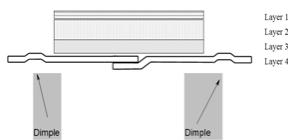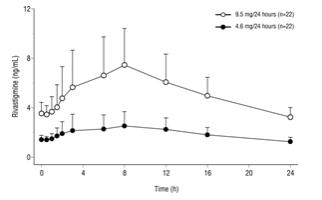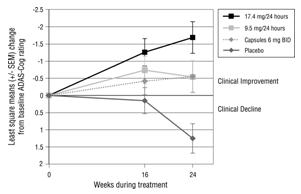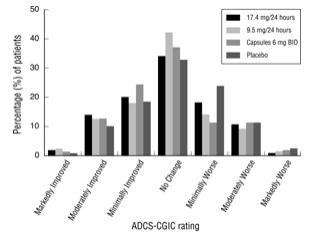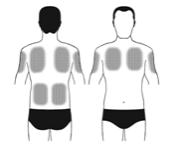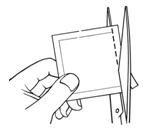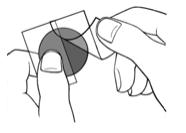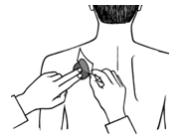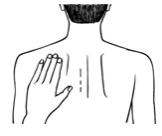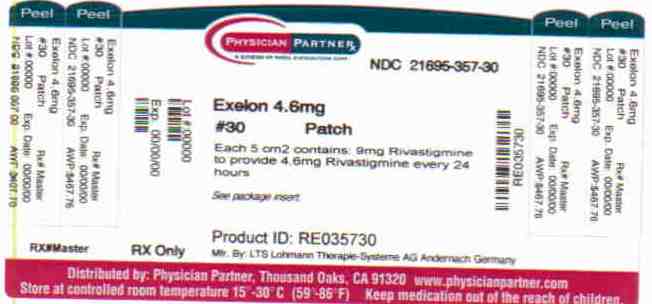 DRUG LABEL: Exelon
NDC: 21695-357 | Form: PATCH, EXTENDED RELEASE
Manufacturer: Rebel Distributors Corp
Category: prescription | Type: HUMAN PRESCRIPTION DRUG LABEL
Date: 20101220

ACTIVE INGREDIENTS: RIVASTIGMINE 4.6 mg/24 [USP'U]
INACTIVE INGREDIENTS: ALPHA-TOCOPHEROL

Exelon

1 INDICATIONS AND USAGE

1.1 Alzheimer’s Disease

Exelon Patch (rivastigmine transdermal system) is indicated for the treatment of mild to moderate dementia of the Alzheimer’s type.

1.2 Parkinson’s Disease Dementia

Exelon Patch (rivastigmine transdermal system) is indicated for the treatment of mild to moderate dementia associated with Parkinson’s disease.

The dementia of Parkinson’s disease is purportedly characterized by impairments in executive function, memory retrieval, and attention in patients with an established diagnosis of Parkinson’s disease. The diagnosis of dementia of Parkinson’s disease can be made reliably in patients in whom a progressive dementia syndrome occurs (without the necessity to document the specific deficits described above) at least 2 years after a diagnosis of Parkinson’s disease has been made, and in whom other causes of dementia have been ruled out.

2 DOSAGE AND ADMINISTRATION

2.1 Alzheimer’s Disease

Table 1: Patch Size, Drug Content and Nominal Delivery Rate
Rivastigmine Nominal Dose | Rivastigmine Content per Exelon Patch | Exelon Patch Size
4.6 mg/24 hours | 9 mg | 5 cm^2
9.5 mg/24 hours | 18 mg | 10 cm^2

2.1.1

Initial Dose

Treatment is started with Exelon Patch 4.6 mg/24 hours.

After a minimum of four weeks of treatment and if well tolerated, this dose should be increased to Exelon Patch 9.5 mg/24 hours, which is the recommended effective dose.

2.1.2

Maintenance Dose

Dose increases should occur only after a minimum of 4 weeks at the previous dose, and only if the previous dose has been well tolerated. The maximum recommended dose is 9.5 mg/24 hours. Higher doses confer no appreciable additional benefit, and are associated with significant increase in the incidence of adverse events [see Adverse Reactions (6)].

If adverse effects (e.g., nausea, vomiting, diarrhea, loss of appetite) cause intolerance during treatment, the patient should be instructed to discontinue treatment for several days and then restart at the same or next lower dose level. If treatment is interrupted for longer than several days, treatment should be reinitiated with the lowest daily dose and titrated as described above [also see Warnings and Precautions (5)].

2.1.3

Switching from Capsules or Oral S

olution

Patients treated with Exelon capsules or oral solution may be switched to Exelon Patch as follows:

A patient who is on a total daily dose of less than 6 mg of oral rivastigmine can be switched to Exelon Patch 4.6 mg/24 hours.

A patient who is on a total daily dose of 6-12 mg of oral rivastigmine may be directly switched to Exelon Patch 9.5 mg/24 hours.

It is recommended to apply the first patch on the day following the last oral dose.

2.1.4

Method of Administration

Exelon Patch should be applied once a day to clean, dry, hairless, intact healthy skin in a place that will not be rubbed against by tight clothing. The upper or lower back is recommended as the site of application because the patch is less likely to be removed by the patient; however, when sites on the back are not accessible the patch can be applied to the upper arm or chest. The patch should not be applied to skin that is red, irritated, or cut. It is recommended that the site of patch application be changed daily to avoid potential irritation, although consecutive patches can be applied to the same anatomic site (e.g., another spot on the upper back).

The patch should be pressed down firmly until the edges stick well. The patch can be used in situations that include bathing and hot weather.

The patch should be replaced with a new one every 24 hours. Do not apply a new patch to that same spot for at least 14 days. Patients and caregivers should be instructed accordingly [see Patient Counseling Information (17)].

2.1.5

Incompatibilities

To prevent interference with the adhesive properties of the patch, the patch should not be applied to a skin area where cream, lotion or powder has recently been applied.

2.1.6

Special Populations

2.1.6.1 Hepatic Impairment

Dosage adjustment is not necessary in hepatically impaired patients, as the dose of drug is individually titrated to tolerability.

2.1.6.2 Renal Impairment

No dose adjustment is necessary for patients with renal impairment.

2.1.6.3 Low Body Weight

Patients with body weight below 50 kg may experience more adverse events and may be more likely to discontinue due to adverse events. Particular caution should be exercised in titrating these patients above the recommended maintenance dose of Exelon Patch 9.5 mg/24 hours.

2.2 Parkinson’s Disease Dementia

See Dosage and Administration (2.1).

3 DOSAGE FORMS AND STRENGTHS

3.1 Dosage Form

Patch.

Each patch is a thin, matrix-type transdermal system consisting of three layers when worn by the patient. A fourth layer, the release liner, covers the adhesive layer prior to use and is removed at the time the system is applied to the skin.

The outside of the backing layer is beige and labeled for each dose as follows:

- “EXELON® PATCH “4.6 mg/24 hours” and “AMCX”

- “EXELON® PATCH “9.5 mg/24 hours” and “BHDI”

3.2 Dosage Strengths

Table 1 summarizes the available strengths and quantity of rivastigmine provided in each patch:

- Each 5 cm^2 patch contains 9 mg rivastigmine base, with
  in vivo release rate of 4.6 mg/24 hours.
- Each 10 cm^2 patch contains 18 mg rivastigmine base, with in vivo release rate of 9.5 mg/24 hours.

For a full list of excipients, see Description (11).

4 CONTRAINDICATIONS

4.1 Hypersensitivity

Exelon Patch (rivastigmine transdermal system) is contraindicated in patients with known hypersensitivity to rivastigmine, other carbamate derivatives, or other components of the formulation [see Description (11)].

5 WARNINGS AND PRECAUTIONS

5.1 Gastrointestinal Adverse Reactions

At higher than recommended doses, Exelon Patch (rivastigmine transdermal system) use is associated with significant gastrointestinal adverse reactions, including nausea, vomiting, diarrhea, anorexia/decreased appetite and weight loss. For this reason, patients administered Exelon Patch should always be started at a dose of 4.6 mg/24 hours and titrated to the maintenance dose of 9.5 mg/24 hours. If treatment is interrupted for longer than several days, treatment should be reinitiated with the lowest daily dose [see Dosage and Administration (2) ] to reduce the possibility of severe vomiting and its potentially serious sequelae (e.g., there has been one post-marketing report of severe vomiting with esophageal rupture following inappropriate reinitiation of treatment with a 4.5-mg dose of an oral formulation after 8 weeks of treatment interruption).

At higher than recommended doses, caregivers should be advised of the high incidence of nausea and vomiting associated with the use of Exelon Patch along with the possibility of anorexia and weight loss. Caregivers should be encouraged to monitor for these adverse events and inform the physician if they occur. It is critical to inform caregivers that if therapy has been interrupted for more than several days, the next dose should not be administered until they have discussed this with the physician.

5.1.1

Nausea and Vomiting

In the controlled clinical trial, 7% of patients treated with Exelon Patch 9.5 mg/24 hours developed nausea, as compared to 23% of patients who received the Exelon capsule at doses up to 6 mg BID and 5% of those who received placebo. In the same clinical trial, 6% of patients treated with Exelon Patch 9.5 mg/24 hours developed vomiting, as compared with 17% of patients who received the Exelon capsule at doses up to 6 mg BID and 3% of those who received placebo. The proportion of patients who discontinued treatment on account of vomiting was 0% of the patients who received Exelon Patch 9.5 mg/24 hours as well as 2% of patients who received the Exelon capsule at doses up to 6 mg BID and 0% of those who received placebo. Vomiting was severe in 0% of patients who received Exelon Patch 9.5 mg/24 hours and 1% of patients who received the Exelon capsule at doses up to 6 mg BID and 0% of those who received placebo.

In the same clinical trial, 21% of patients treated with the higher dose of Exelon Patch 17.4 mg/24 hours developed nausea, 19% developed vomiting, and the proportion of these patients who discontinued treatment on account of vomiting was 2%. Vomiting was severe in 1% of patients treated with Exelon Patch 17.4 mg/24 hours.

5.1.2

Weight Loss

In the controlled clinical trial, the proportion of patients who had weight loss equal to or greater than 7% of their baseline weight was 8% of those treated with Exelon Patch 9.5 mg/24 hours, 11% of patients who received the Exelon capsule at doses up to 6 mg BID and 6% of those who received placebo.

In the same clinical trial, 12% of those treated with 17.4 mg/24 hours had weight loss equal to or greater than 7% of their baseline weight. It is not clear how much of the weight loss was associated with anorexia, nausea, vomiting, and the diarrhea associated with the drug.

5.1.3

Diarrhea

In the controlled clinical trial, 6% of patients treated with Exelon Patch 9.5 mg/24 hours developed diarrhea, as compared with 5% of patients who received the Exelon capsule at doses up to 6 mg BID, 10% of those treated with 17.4 mg/24 hours and 3% of those who received placebo.

5.1.4

Anorexia/Decreased Appetite

In the controlled clinical trial, 3% of patients treated with Exelon Patch 9.5 mg/24 hours were recorded as developing decreased appetite or anorexia, as compared with 9% of patients who received the Exelon capsule at doses up to 6 mg BID, 9% of those treated with Exelon Patch 17.4 mg/24 hours and 2% of those who received placebo.

5.1.5

Peptic Ulcers/Gastrointestinal Bleeding

Because of their pharmacological action, cholinesterase inhibitors may be expected to increase gastric acid secretion due to increased cholinergic activity. Therefore, patients should be monitored closely for symptoms of active or occult gastrointestinal bleeding, especially those at increased risk for developing ulcers, e.g., those with a history of ulcer disease or those receiving concurrent nonsteroidal anti-inflammatory drugs (NSAIDs). Clinical studies of Exelon have shown no significant increase, relative to placebo, in the incidence of either peptic ulcer disease or gastrointestinal bleeding.

5.2

Anesthesia

Exelon, as a cholinesterase inhibitor, is likely to exaggerate succinylcholine-type muscle relaxation during anesthesia.

5.3

Cardiovascular Conditions

Drugs that increase cholinergic activity may have vagotonic effects on heart rate (e.g., bradycardia). The potential for this action may be particularly important to patients with sick sinus syndrome or other supraventricular cardiac conduction conditions. In clinical trials, Exelon was not associated with any increased incidence of cardiovascular adverse events, heart rate or blood pressure changes, or ECG abnormalities.

5.

4

Genitourinary Conditions

Although this was not observed in clinical trials of Exelon, drugs that increase cholinergic activity may cause urinary obstruction.

5.

5

Neurological Conditions

5.5.1

Seizures

Drugs that increase cholinergic activity are believed to have some potential for causing seizures. However, seizure activity also may be a manifestation of Alzheimer's disease.

5.5.2

Extrapyramidal Symptoms

Like other cholinomimetics, rivastigmine may exacerbate or induce extrapyramidal symptoms. Worsening of parkinsonian symptoms, particularly tremor, has been observed in patients with dementia associated with Parkinson’s disease who were treated with Exelon capsules.

5.

6

Pulmonary Conditions

Like other drugs that increase cholinergic activity, Exelon should be used with care in patients with a history of asthma or obstructive pulmonary disease.

5.

7

Effects on Ability to Drive and Use Machines

Dementia may cause gradual impairment of driving performance or compromise the ability to use machinery. The administration of rivastigmine may also result in adverse events that are detrimental to these functions. Thus, the ability to continue driving or operating machinery should be routinely evaluated by the treating physician.

5.

8

Special Populations

5.8.1

Low Body Weight

Patients with body weight below 50 kg may experience more adverse events and may be more likely to discontinue due to adverse events. Particular caution should be exercised in titrating these patients above the recommended maintenance dose of the Exelon Patch 9.5 mg/24 hours.

6 ADVERSE REACTIONS

Significant gastrointestinal adverse reactions including nausea, vomiting, anorexia, and weight loss have been reported with the Exelon Patch at higher than recommended doses [see Warnings and Precautions (5.1)].

6.1 Incidence in

C

ontrolled

C

linical

T

rial in Alzheimer’s Disease

6.1.1

Associated with

D

iscontinuation of

T

reatment

In the single controlled clinical trial of Exelon Patch [see Clinical Studies (14)], which randomized a total of 1195 patients, the proportions of patients in the Exelon Patch 9.5 mg/24 hours, Exelon Patch 17.4 mg/24 hours, Exelon capsules 6 mg BID, and placebo groups who discontinued treatment due to adverse events were 9.6%, 8.6%, 8.1%, and 5.0%, respectively.

The most common adverse events in the Exelon Patch-treated groups that led to treatment discontinuation in this study were nausea and vomiting. The proportions of patients who discontinued treatment due to nausea were 0.7%, 1.7%, 1.7%, and 1.3% in the Exelon Patch 9.5 mg/24 hours, Exelon Patch 17.4 mg/24 hours, Exelon capsules 6 mg BID, and placebo groups, respectively. The proportions of patients who discontinued treatment due to vomiting were 0%, 1.7%, 2.0%, and 0.3% in the Exelon Patch 9.5 mg/24 hours, Exelon Patch 17.4 mg/24 hours, Exelon capsules 6 mg BID, and placebo groups, respectively.

6.1.2

Most Commonly Observed Adverse E

vents

The most commonly observed adverse events seen in patients administered Exelon Patch in the controlled clinical trial, defined as those occurring at a frequency of at least 5% in the 9.5 mg/24 hours group and at a frequency at least as high as in the placebo group are largely predicted by the cholinergic effects of Exelon. These are nausea, vomiting, and diarrhea. All these events were more common at the higher Exelon Patch dose of 17.4 mg/24 hours than at a dose of 9.5 mg/24 hours.

6.1.3

Adverse Events Observed at an I

ncidence of ≥2%

The following table lists treatment-emergent adverse events that were seen at an incidence of ≥2% in either Exelon Patch-treated group in the controlled clinical trial and for which the rate of occurrence was greater for patients treated with that dose of Exelon Patch than for those treated with placebo. The prescriber should be aware that these frequencies cannot be used to predict the frequency of adverse events in the course of usual medical practice when patient characteristics and other factors may differ from those prevailing during clinical studies. Similarly, the cited frequencies cannot be directly compared with frequencies obtained from other clinical investigations involving different treatments, uses, or investigators. An inspection of these frequencies, however, does provide the prescriber with one basis by which to estimate the relative contribution of drug and non-drug factors to the adverse event incidences in the population studied.

Table 2: Adverse Events Observed with a Frequency of ≥2% and Occurring with a Rate Greater Than Placebo
 | Exelon Patch 9.5 mg/ 24 hours n (%) | Exelon Patch 17.4 mg/ 24 hours n (%) | Exelon capsule 6 mg BID n (%) | Placebo n (%)
Total Patients Studied Total Number of Patients with AEs | 291 147 (51) | 303 200 (66) | 294 186 (63) | 302 139 (46)
Nausea | 21 (7) | 64 (21) | 68 (23) | 15 (5)
Vomiting | 18 (6) | 57 (19) | 50 (17) | 10 (3)
Diarrhea | 18 (6) | 31 (10) | 16 (5) | 10 (3)
Depression | 11 (4) | 12 (4) | 13 (4) | 4 (1)
Headache | 10 (3) | 13 (4) | 18 (6) | 5 (2)
Anxiety | 9 (3) | 8 (3) | 5 (2) | 4 (1)
Anorexia/ Decreased | 9 (3) | 27 (9) | 26 (9) | 6 (2)
Weight Decreased | 8 (3) | 23 (8) | 16 (5) | 4 (1)
Dizziness | 7 (2) | 21 (7) | 22 (7) | 7 (2)
Abdominal Pain | 7 (2) | 11 (4) | 4 (1) | 2 (1)
Urinary Tract Infection | 6 (2) | 5 (2) | 4 (1) | 3 (1)
Asthenia | 5 (2) | 9 (3) | 17 (6) | 3 (1)
Fatigue | 5 (2) | 7 (2) | 2 (1) | 4 (1)
Insomnia | 4 (1) | 12 (4) | 6 (2) | 6 (2)
Abdominal Pain Upper | 3 (1) | 8 (3) | 6 (2) | 6 (2)
Vertigo | 0 (0) | 7 (2) | 4 (1) | 3 (1)

6.1.4

Incidenc

e of Application Site Reactions

The vast majority of patients participating in the controlled clinical trial had either no observed skin irritation or mild to moderate skin reactions. The incidence of severe reactions was very low regardless of administered dosage.

6.2

Other Adverse Events O

bserved

D

uring

C

linical

T

rials

Exelon Patch has been administered to 1071 patients with Alzheimer’s disease during clinical trials worldwide. Of these, 869 patients have been treated for at least 3 months, 706 patients have been treated for at least 6 months, and 212 patients have been treated for 1 year.

Treatment-emergent signs and symptoms that occurred during 1 controlled and 4 open-label trials in North America, Europe, Latin America, Asia and Japan were recorded as adverse events by the clinical investigators using terminology of their own choosing.

To provide an overall estimate of the proportion of individuals having similar types of events, the events were grouped into a smaller number of standardized categories using the MedDRA dictionary, and event frequencies were calculated across all studies. These categories are used in the listing below. The frequencies represent the proportion of 1071 patients from these trials who experienced that event while receiving Exelon Patch. All patch doses are pooled.

All adverse events occurring in at least 1 patient (approximately 0.1%) are included, except for those already listed elsewhere in labeling, too general to be informative, or relatively minor events.

Events are classified by system organ class and listed using the following definitions: Frequent – those occurring in at least 1/100 patients; Infrequent – those occurring in 1/100 to 1/1,000 patients. These adverse events are not necessarily related to Exelon Patch treatment and in most cases were observed at a similar frequency in placebo-treated patients in the controlled studies.

Blood and Lymphatic System Disorders: Frequent : Anemia.

Cardiac Disorders: Infrequent : Angina pectoris, cardiac failure, bradycardia, atrial fibrillation, supraventricular extrasystoles, myocardial infarction, tachycardia, arrhythmia, atrioventricular block.

Ear and Labyrinth Disorders: Infrequent : Tinnitus.

Eye Disorders: Infrequent : Cataract, glaucoma, vision blurred.

Gastrointestinal System: Frequent : Constipation, gastritis. Infrequent : Gastroesophageal reflux disease, hematochezia, peptic ulcer, hematemesis, pancreatitis, salivary hypersecretion.

General Disorders and Administration Site Conditions: Infrequent : Application site dermatitis, application site irritation, peripheral edema, chest pain, application site eczema, hyperpyrexia.

Hepatobiliary Disorders: Infrequent : Cholecystitis.

Infections and Infestations: Frequent : Nasopharyngitis, pneumonia. Infrequent : Diverticulitis.

Injury, Poisoning and Procedural Complications: Frequent : Fall. Infrequent : Hip fracture, subdural hematoma.

Investigations: Infrequent : Blood creatine phosphokinase increased, lipase increased, blood amylase increased, electrocardiogram QT prolonged.

Metabolic and Nutritional Disorders: Frequent : Dehydration Infrequent : Hyperlipidemia, hypokalemia, hyponatremia.

Musculoskeletal and Connective Tissue Disorders: Infrequent: Arthralgia, muscle spasms, myalgia.

Nervous System Disorders: Frequent : Tremor. Infrequent : Migraine, parkinsonism, epilepsy.

Psychiatric Disorders: Infrequent : Delusion.

Renal and Urinary Disorders: Frequent : Urinary incontinence. Infrequent : Pollakiuria, hematuria, nocturia, renal failure.

Reproductive System and Breast Disorders: Infrequent : Benign prostatic hyperplasia.

Respiratory, Thoracic, and Mediastinal Disorders: Infrequent : Dyspnea, bronchospasm, chronic obstructive pulmonary disease.

Skin and Subcutaneous Tissue Disorders: Frequent : Pruritus. Infrequent : Erythema, eczema, dermatitis, rash erythematous, skin ulcer.

Vascular Disorders: Infrequent : Hypotension.

7 DRUG INTERACTIONS

No specific interaction studies have been conducted with Exelon Patch (rivastigmine transdermal system).

7.1

Effect of Exelon on the Metabolism of Other Drugs

Rivastigmine is primarily metabolized through hydrolysis by esterases. Minimal metabolism occurs via the major cytochrome P450 isoenzymes. Based on in-vitro studies, no pharmacokinetic drug interactions with drugs metabolized by the following isoenzyme systems are expected: CYP1A2, CYP2D6, CYP3A4/5, CYP2E1, CYP2C9, CYP2C8, or CYP2C19.

No pharmacokinetic interaction was observed between rivastigmine taken orally and digoxin, warfarin, diazepam or fluoxetine in studies in healthy volunteers. The increase in prothrombin time induced by warfarin is not affected by administration of rivastigmine.

7.2

Effect of Other Drugs on the Metabolism of Exelon

Drugs that induce or inhibit CYP450 metabolism are not expected to alter the metabolism of rivastigmine.

Population PK analysis with a database of 625 patients showed that the pharmacokinetics of rivastigmine taken orally were not influenced by commonly prescribed medications such as antacids (n=77), antihypertensives (n=72), ß-blockers (n=42), calcium channel blockers (n=75), antidiabetics (n=21), nonsteroidal anti-inflammatory drugs (n=79), estrogens (n=70), salicylate analgesics (n=177), antianginals (n=35) and antihistamines (n=15).

7.3

Use with Anticholinergics

,

C

holinomimetics and

O

ther

Cholinesterase I

nhibitors

In view of its pharmacodynamic effects, rivastigmine should not be given concomitantly with other cholinomimetic drugs and might interfere with the activity of anticholinergic medications. A synergistic effect may be expected when cholinesterase inhibitors are given concurrently with succinylcholine, similar neuromuscular blocking agents or cholinergic agonists such as bethanechol.

8 USE IN SPECIFIC POPULATIONS

8.1 Pregnancy

8.1.1

Pregnancy Category B

There are no adequate or well-controlled studies in pregnant women. Because animal reproduction studies are not always predictive of human response, Exelon Patch should be used during pregnancy only if the potential benefit outweighs the potential risk to the fetus. No dermal reproduction studies in animals have been conducted. Oral reproduction studies conducted in pregnant rats at doses up to 2.3 mg base/kg/day and in pregnant rabbits at doses up to 2.3 mg base/kg/day revealed no evidence of teratogenicity. Studies in rats showed slightly decreased fetal/pup weights, usually at doses causing some maternal toxicity.

8.

3

Nursing Mothers

Milk transfer studies in animals have not been conducted with dermal rivastigmine. In rats given rivastigmine orally, concentrations of rivastigmine plus metabolites were approximately two times higher in milk than in plasma. It is not known whether rivastigmine is excreted in human breast milk. Exelon Patch (rivastigmine transdermal system) has no indication for use in nursing mothers.

8.

4

Pediatric Use

There are no adequate and well-controlled trials documenting the safety and efficacy of Exelon in any illness occurring in children.

8.

5

Geriatric Use

Age had no impact on the exposure to rivastigmine in Alzheimer’s disease patients treated with Exelon Patch.

8.

6

Hepatic Disease

No pharmacokinetic study was conducted with Exelon Patch in subjects with hepatic impairment. Following a single 3-mg dose, mean oral clearance of rivastigmine was 60% lower in hepatically impaired patients (n=10, biopsy proven) than in healthy subjects (n=10). After multiple 6-mg BID oral dosing, the mean clearance of rivastigmine was 65% lower in mild (n=7, Child-Pugh score 5-6) and moderate (n=3, Child-Pugh score 7-9) hepatically impaired patients (biopsy proven, liver cirrhosis) than in healthy subjects (n=10). Dosage adjustment is not necessary in hepatically impaired patients as the dose of drug is individually titrated to tolerability.

8.

7

Renal Disease

No study was conducted with Exelon Patch in subjects with renal impairment. Following a single 3-mg dose, mean oral clearance of rivastigmine is 64% lower in moderately impaired renal patients (n=8, GFR=10-50 mL/min) than in healthy subjects (n=10, GFR greater than or equal to 60 mL/min); Cl/F=1.7 L/min (cv=45%) and 4.8 L/min (cv=80%), respectively. In severely impaired renal patients (n=8, GFR less than 10 mL/min), mean oral clearance of rivastigmine is 43% higher than in healthy subjects (n=10, GFR greater than or equal to 60 mL/min); Cl/F=6.9 L/min and 4.8 L/min, respectively. For unexplained reasons, the severely impaired renal patients had a higher clearance of rivastigmine than moderately impaired patients. However, dosage adjustment may not be necessary in renally impaired patients as the dose of the drug is individually titrated to tolerability.

8.

8

Low Body Weight

Rivastigmine exposure is higher in subjects with low body weight. Compared to a patient with a body weight of 65 kg, the rivastigmine steady-state concentrations in a patient with a body weight of 35 kg would be approximately doubled, while for a patient with a body weight of 100 kg the concentrations would be approximately halved. This suggests special attention should be given to patients with very low body weight during up-titration [see Dosage and Administration (2)].

8.

9

Gender and Race

No specific pharmacokinetic study was conducted to investigate the effect of gender and race on the disposition of Exelon, but a population pharmacokinetic analysis indicates that gender (n=277 males and 348 females) and race (n=575 White, 34 Black, 4 Asian, and 12 Other) did not affect the clearance of Exelon administered orally. Similar results were seen with analyses of pharmacokinetic data obtained after the administration of Exelon Patch.

8.

10

Nicotine Use

Population pharmacokinetic analysis showed that nicotine use increases the oral clearance of rivastigmine by 23% (n=75 Smokers and 549 Nonsmokers). No dose adjustment is necessary as the dose of the drug is individually titrated to tolerability.

10 OVERDOSAGE

Because strategies for the management of overdose are continually evolving, it is advisable to contact a Poison Control Center to determine the latest recommendations for the management of an overdose of any drug. As in any case of overdose, general supportive measures should be utilized.

As rivastigmine has a plasma half-life of about 3.4 hours after patch administration and a duration of acetylcholinesterase inhibition of about 9 hours, it is recommended that in cases of asymptomatic overdose the patch should be immediately removed and no further patch should be applied for the next 24 hours.

As in any case of overdose, general supportive measures should be utilized. Overdosage with cholinesterase inhibitors can result in cholinergic crisis characterized by severe nausea, vomiting, salivation, sweating, bradycardia, hypotension, respiratory depression, collapse and convulsions. Increasing muscle weakness is a possibility and may result in death if respiratory muscles are involved. Atypical responses in blood pressure and heart rate have been reported with other drugs that increase cholinergic activity when coadministered with quaternary anticholinergics such as glycopyrrolate. Due to the short plasma elimination half-life of rivastigmine after patch administration, dialysis (hemodialysis, peritoneal dialysis, or hemofiltration) would not be clinically indicated in the event of an overdose.

In overdose accompanied by severe nausea and vomiting, the use of antiemetics should be considered. In a documented case of an oral 46-mg overdose with Exelon, the patient experienced vomiting, incontinence, hypertension, psychomotor retardation, and loss of consciousness. The patient fully recovered within 24 hours and conservative management was all that was required for treatment.

There are currently no data on overdose with Exelon Patch (rivastigmine transdermal system).

11 DESCRIPTION

Exelon Patch (rivastigmine transdermal system) is a reversible cholinesterase inhibitor and is known chemically as (S)- 3-[1-(dimethylamino) ethyl]phenyl ethylmethylcarbamate. It has an empirical formula of C14H22N2O2 as the base and a molecular weight of 250.34 (as the base). Rivastigmine is a viscous, clear, and colorless to yellow to very slightly brown liquid that is sparingly soluble in water and very soluble in ethanol, acetonitrile, n-octanol and ethyl acetate.

The distribution coefficient at 37°C in n-octanol/phosphate buffer solution pH 7 is 4.27.

Exelon Patch is for transdermal administration. The patch comprises a four-layer laminate containing the backing layer, drug matrix, adhesive matrix and overlapping release liner. The release liner is removed and discarded prior to use. See Figure 1 for a detailed illustration.

Layer 1 | Backing Film
Layer 2 | Drug Product (Acrylic) Matrix
Layer 3 | Adhesive (Silicone) Matrix
Layer 4 | Release Liner (removed at time of use)

Excipients within the formulation include acrylic copolymer, poly(butylmethacrylate, methylmethacrylate), silicone adhesive applied to a flexible polymer backing film, silicone oil, and vitamin E.

12 CLINICAL PHARMACOLOGY

12.1 Mechanism of Action

Pathological changes in dementia of the Alzheimer’s type and dementia associated with Parkinson’s disease involve cholinergic neuronal pathways that project from the basal forebrain to the cerebral cortex and hippocampus. These pathways are thought to be intricately involved in memory, attention, learning, and other cognitive processes. While the precise mechanism of action for rivastigmine is unknown, it is postulated to exert its therapeutic effect by enhancing cholinergic function. This is accomplished by increasing the concentration of acetylcholine through reversible inhibition of its hydrolysis by cholinesterase. If this proposed mechanism is correct, the effect of rivastigmine may lessen as the disease process advances and fewer cholinergic neurons remain functionally intact. There is no evidence that rivastigmine alters the course of the underlying dementing process.

12.2 Pharmacodynamics

After a 6-mg oral dose of rivastigmine in humans, anticholinesterase activity is present in CSF for about 10 hours, with a maximum inhibition of about 60% 5 hours after dosing.

In-vitro and in-vivo studies demonstrate that the inhibition of cholinesterase by rivastigmine is not affected by the concomitant administration of memantine, an N-methyl-D-aspartate receptor antagonist.

12.3 Pharmacokinetics

12.3.1

Absorption

After the first dose, there is a lag time of 0.5-1 hour in the absorption of rivastigmine from Exelon Patch (rivastigmine transdermal system). Concentrations then rise slowly typically reaching a maximum after 8 hours, although maximum values (Cmax) are often reached at later times as well (10-16 hours). After the peak, plasma concentrations slowly decrease over the remainder of the 24-hour period of application. At steady state, trough levels are approximately 60-80% of peak levels. Fluctuation (between Cmax and Cmin) is lower for Exelon Patch than for the oral formulation. Exelon Patch 9.5 mg/24 hours exhibited exposure approximately the same as that provided by an oral dose of 6 mg twice daily (i.e., 12 mg/day).

Figure 2: Rivastigmine Plasma Concentrations Following Dermal 24-Hour Patch Application

Inter-subject variability in exposure was lower (43-49%) for the Exelon Patch formulation as compared with the oral formulations (73-103%).

A relationship between drug exposure at steady state (rivastigmine and metabolite NAP226-90) and bodyweight was observed in Alzheimer’s dementia patients. Compared to a patient with a body weight of 65 kg, the rivastigmine steady-state concentrations in a patient with a body weight of 35 kg are approximately doubled, while for a patient with a body weight of 100 kg the concentrations are approximately halved. The effect of body weight on drug exposure suggests special attention to patients with very low body weight during up-titration [see Dosage and Administration (2)].

Over a 24-hour dermal application, approximately 50% of the drug load is released from the system.

Exposure (AUC∞) to rivastigmine (and metabolite NAP266-90) was highest when the patch was applied to the upper back, chest, or upper arm. Two other sites (abdomen and thigh) could be used if none of the three other sites is available, but the practitioner should keep in mind that the rivastigmine plasma exposure associated with these sites was approximately 20-30% lower.

There was no relevant accumulation of rivastigmine or the metabolite NAP226-90 in plasma in patients with Alzheimer’s disease upon multiple dosing.

12.3.2

Distribution

Rivastigmine is weakly bound to plasma proteins (approximately 40%) over the therapeutic range. It readily crosses the blood-brain barrier, reaching CSF peak concentrations in 1.4-2.6 hours. It has an apparent volume of distribution in the range of 1.8-2.7 L/kg.

12.3.3

Metabolism

Rivastigmine is extensively metabolized primarily via cholinesterase-mediated hydrolysis to the decarbamylated metabolite NAP226-90. In vitro, this metabolite shows minimal inhibition of acetylcholinesterase (less than 10%). Based on evidence from in-vitro and animal studies, the major cytochrome P450 isoenzymes are minimally involved in rivastigmine metabolism.

The metabolite-to-parent AUC∞ ratio was about 0.7 after Exelon Patch application versus 3.5 after oral administration, indicating that much less metabolism occurred after dermal treatment. Less NAP226-90 is formed following patch application, presumably because of the lack of presystemic (hepatic first pass) metabolism. Based on in-vitro studies, no unique metabolic routes were detected in human skin.

12.3.4

Elimination

Renal excretion of the metabolites is the major route of elimination. Unchanged rivastigmine is found in trace amounts in the urine. Following administration of ^14C-rivastigmine, renal elimination was rapid and essentially complete (greater than 90%) within 24 hours. Less than 1% of the administered dose is excreted in the feces. The apparent elimination half-life in plasma is approximately 3 hours after patch removal. Renal clearance was approximately
2.1-2.8 L/hr.

13 NONCLINICAL TOXICOLOGY

13.1 Carcinogenesis, Mutagenesis, Impairment of Fertility

In oral carcinogenicity studies conducted at doses up to 1.1 mg base/kg/day in rats and 1.6 mg base/kg/day in mice, rivastigmine was not carcinogenic.

In a dermal carcinogenicity study conducted at doses up to 0.75 mg base/kg/day in mice, rivastigmine was not carcinogenic. The mean rivastigmine plasma exposure (AUC) at this dose was 0.3-0.4 times that observed in Alzheimer’s disease patients at the recommended clinical dose (one Exelon Patch 9.5 mg/24 hours).

Rivastigmine was clastogenic in two in-vitro assays in the presence, but not the absence, of metabolic activation. It caused structural chromosomal aberrations in V79 Chinese hamster lung cells and both structural and numerical (polyploidy) chromosomal aberrations in human peripheral blood lymphocytes. Rivastigmine was not genotoxic in three in-vitro assays: the Ames test, the unscheduled DNA synthesis (UDS) test in rat hepatocytes (a test for induction of DNA repair synthesis), and the HGPRT test in V79 Chinese hamster cells. Rivastigmine was not clastogenic in the in-vivo mouse micronucleus test.

No fertility or reproduction studies have been conducted in animals treated with dermal rivastigmine. Rivastigmine had no effect on fertility or reproductive performance in rats at oral doses up to 1.1 mg base/kg/day.

14 CLINICAL STUDIES

The effectiveness of the Exelon Patch (rivastigmine transdermal system) in Alzheimer’s disease and dementia associated with Parkinson’s disease was based on the results of a single controlled trial in patients with Alzheimer’s disease (see below) as well as on three controlled trials of the immediate-release capsule in Alzheimer’s disease and one controlled trial in dementia associated with Parkinson’s disease (see package insert for the Exelon capsules and oral solution for details).

14.1

International 24-Week Study of Exelon

Patch (rivastigmine

transdermal

system)

This was a randomized double-blind clinical investigation in patients with Alzheimer’s disease [diagnosed by NINCDS-ADRDA and DSM-IV criteria, Mini-Mental Status Examination (MMSE) score ≥10 and ≤20]. The mean age of patients participating in this trial was 74 years with a range of 50-90 years. Approximately 67% of patients were women and 33% were men. The racial distribution was Caucasian 75%, Black 1%, Oriental 9% and Other Races 15%.

14.2

Study Outcome Measures

The effectiveness of the Exelon Patch (rivastigmine transdermal system) was evaluated in this study using a dual outcome assessment strategy.

The ability of the Exelon Patch to improve cognitive performance was assessed with the cognitive subscale of the Alzheimer’s Disease Assessment Scale (ADAS-Cog), a multi-item instrument that has been extensively validated in longitudinal cohorts of Alzheimer’s disease patients. The ADAS-Cog examines selected aspects of cognitive performance including elements of memory, orientation, attention, reasoning, language and praxis. The ADAS-Cog scoring range is from 0-70, with higher scores indicating greater cognitive impairment. Elderly normal adults may score as low as 0 or 1, but it is not unusual for non-demented adults to score slightly higher.

The ability of the Exelon Patch to produce an overall clinical effect was assessed using the Alzheimer’s Disease Cooperative Study - Clinical Global Impression of Change (ADCS-CGIC). The ADCS-CGIC is a more standardized form of CIBIC-Plus and is also scored as a seven-point categorical rating, ranging from a score of 1, indicating “markedly improved”, to a score of 4, indicating “no change” to a score of 7, indicating “marked worsening”.

14.3

Study Results

In this study, 1195 patients were randomized to one of the following 4 treatments: Exelon Patch 9.5 mg/24 hours, Exelon Patch 17.4 mg/24 hours, Exelon capsules in a dose of 6 mg BID, or placebo. This 24-week study was divided into a 16-week titration phase followed by an 8-week maintenance phase. In the active treatment arms of this study, doses below the target dose were permitted during the maintenance phase in the event of poor tolerability.

14.3.1

Effects on the ADAS-Cog

Figure 3 illustrates the time course for the change from baseline in ADAS-Cog scores for all 4 treatment groups over the 24-week study. At 24 weeks, the mean differences in the ADAS-Cog change scores for the Exelon-treated patients, compared to the patients on placebo, were 1.8, 2.9, and 1.8 units for the Exelon Patch 9.5 mg/24 hours, Exelon Patch 17.4 mg/24 hours, and Exelon capsule 6 mg BID groups, respectively. The difference between each of these groups and placebo was statistically significant.

14.3.2

Effects on the ADCS-CGIC

Figure 4 is a histogram of the distribution of patients’ scores on the ADCS-CGIC for all 4 treatment groups.

At 24 weeks, the mean difference in the ADCS-CGIC scores for the comparison of patients in each of the Exelon-treated groups with the patients on placebo was 0.2 units. The difference between each of these groups and placebo was statistically significant.

Figure 3: Time Course of the Change from Baseline in ADAS-Cog Score for Patients Observed at Each Time Point

Figure 4: Distribution of ADCS-CGIC Scores for Patients Completing the Study

16 HOW SUPPLIED/STORAGE AND HANDLING

Patch 4.6 mg/24 hours

Each patch of 5 cm^2 contains 9 mg rivastigmine base with in-vivo release rate of 4.6 mg/24 hours.

Carton of 30………………………NDC 21695-357-30

Store at 25°C (77°F); excursions permitted to 15-30°C
(59-86°F) [see USP Controlled Room Temperature].

Keep Exelon Patch (rivastigmine transdermal system) in the individual sealed pouch until use.

Used systems should be folded, with the adhesive surfaces pressed together, and discarded safely.

Each pouch contains one patch.

17 PATIENT COUNSELING INFORMATION

17.1

General

Patient information is printed in section 17.8. To assure safe and effective use of Exelon Patch, this information and instructions provided in the patient information section should be discussed with patients.

17.

2

Importance of Correct Usage

Patients or caregivers should be informed of the importance of applying the correct dose on the correct part of their body. They should be instructed to rotate the application site in order to minimize skin irritation. The same site should not be used within 14 days. Exelon Patch should be replaced every 24 hours and the time of day should be consistent. It may be helpful for this to be part of a daily routine, such as the daily bath or shower.

Patients or caregivers should be told to avoid exposure of the patch to external heat sources (excess sunlight, saunas, solariums) for long periods of time.

17.3

Discarding Used Patch

es

Patients or caregivers should be instructed to fold the patch in half after use. Return the used patch to its original pouch and discard it out of the reach and sight of children and pets. They should also be informed that drug still remains in the patch after 24-hour usage. They should be instructed to avoid eye contact and to wash their hands after handling the patch.

17.4

Concomitant Use of Drugs with Cholinergic Action

Patients or caregivers should be told that while wearing Exelon Patch they should not be taking Exelon capsules or Exelon oral solution or other drugs with cholinergic effects.

17.5

Gastrointestinal Adverse Events

Patients or caregivers should be informed of the potential gastrointestinal adverse events such as nausea, vomiting and diarrhea. Patients and caregivers should be instructed to observe for these adverse reactions at all times, in particular when treatment is initiated or the dose is increased. Patients and caregivers should be instructed to inform their physician if these adverse events persist as a dose adjustment/
reduction may be required.

17.

6

Monitoring the Patient’s Weight

Patients or caregivers should be informed that Exelon Patch may affect the patient’s appetite and/or the patient’s weight. Any loss of appetite or weight reduction needs to be monitored.

17.7

Missed Doses

If the patient has missed a dose, he/she should be instructed to apply a new patch immediately. They may apply the next patch at the usual time the next day. Patients should not apply two patches to make up for one missed.

If treatment has been missed for several days, the patient or caregiver should be informed to restart treatment with the starting patch dose of 4.6 mg/24 hours. Titration to the next patch dose should proceed after 4 weeks [see Dosage and Administration (2.1)].

17.

8

FDA-

A

pproved

P

atient

L

abeling

What is Exelon Patch and what it is used for ?

Exelon belongs to a class of substances called cholinesterase inhibitors. It is used for the treatment of memory disorders in patients with Alzheimer’s disease or with Parkinson’s disease.

Before you apply Exelon Patch :

Carefully follow all instructions given to you by your doctor, even if they differ from the information contained in this leaflet.

Read the following information before you apply Exelon Patch.

Do not apply Exelon Patch in the following cases:

If you know that you are allergic (hypersensitive) to rivastigmine (the active substance in Exelon Patch) or to any of the other ingredients of Exelon Patch [see Description (11)].

If you have ever had an allergic reaction to a similar type of medicine.

If this applies to you, tell your doctor without applying Exelon Patch.

Take special care with Exelon Patch if:

- You have, or ever had an irregular heartbeat.
- You have, or ever had an active stomach ulcer.
- You have, or ever had difficulties in passing urine.
- You have, or ever had seizures.
- You have, or ever had asthma or a severe respiratory disease.
- You suffer from trembling.
- You have a low body weight.
- You have impaired liver function.

If any of these apply to you, your doctor may need to monitor you more closely while you are on this medicine.

If you have not been applying Exelon Patch for several days do not apply the next patch until you have talked to your doctor.

Exelon Patch with food and drink:

Food or drink does not affect Exelon Patch because rivastigmine enters your bloodstream through your skin.

Exelon Patch and older people:

Exelon Patch can be used by patients over the age of 65.

Exelon Patch and children:

The use of Exelon Patch in children is not recommended.

Pregnant women:

Tell your doctor if you are pregnant or planning to become pregnant. In the event of pregnancy, the benefits of Exelon Patch must be assessed against the possible effects on your unborn child. Ask your doctor or pharmacist for advice before taking any medicine during pregnancy.

Breast-feeding mothers:

You should not breast-feed during treatment with Exelon Patch. Ask your doctor or pharmacist for advice before taking any medicine while you are breast-feeding.

Driving and using machines:

Your doctor will tell you whether your illness allows you to drive vehicles and use machines safely. Exelon Patch may cause dizziness and drowsiness, mainly at the start of treatment or when increasing the dose. If you feel dizzy or drowsy, do not drive, use machines or perform any other tasks that require your attention.

Taking other medicines:

Tell your doctor or pharmacist about any other medicines you are taking or have recently taken, including any you get without a prescription.

Exelon Patch should not be given together with other medicines with similar effects (cholinomimetic agents) or with anticholinergic medicines.

If you need to have surgery while using Exelon Patch, you should inform your doctor because Exelon Patch may exaggerate the effects of some muscle relaxants during anesthesia.

How to use Exelon Patch :

Follow all instructions given to you by your doctor carefully, even if they differ from the ones given in this leaflet.

This medicine must not be given to children.

Do not eat Exelon Patch.

You must remove Exelon Patch from the previous day before applying a new one. Do not cut the patch into pieces.

How to start treatment:

Your doctor will tell you which Exelon Patch is suitable for you. Treatment usually starts with Exelon Patch 4.6 mg/24 hours, and after several weeks many patients move to Exelon Patch 9.5 mg/24 hours as the usual daily dose. Apply the correct dose as directed by your doctor. The patch should be replaced by a new one after 24 hours.

During the course of treatment, your doctor may adjust the dose to suit your individual needs.

If you have not been applying Exelon Patch for several days, do not apply the next patch before you have talked to your doctor.

Where to apply Exelon Patch :

Apply the patch to the upper or lower back if it is likely that the patient will remove it. If this is not a concern, the patch can be applied instead to the upper arm or chest. Avoid places where the patch can be rubbed off by tight clothing.

Before you apply Exelon Patch, make sure that your skin is:

- clean, dry and hairless
- free of any powder, oil, moisturizer, or lotion (that could keep the patch from sticking to your skin properly)
- free of cuts, rashes and/or irritations

When changing the patch, apply a new patch to a different spot of skin (for example on the right side of the body one day, then on the left side the next day). Do not apply a new patch to that same spot for at least 14 days. Apply the correct dose as directed by your doctor. The patch should be replaced by a new one after 24 hours.

How to apply Exelon Patch:

The patch is a thin, opaque, plastic patch that sticks to the skin. Each patch is sealed in a pouch that protects it until you are ready to put it on. Do not open the pouch or remove a patch until just before you apply it.

Cut the pouch along the dotted line and remove the patch.

The patch should not be cut or folded sharply.

A protective liner covers the adhesive side of the patch. Peel off one side of the protective liner and do not touch the sticky part of the patch with the fingers.

Put the sticky side of the patch on the upper or lower back, upper arm or chest and then peel off the second side of the protective liner.

Press the patch firmly in place with the hand to make sure that the edges stick well.

You may write (e.g., the day of the week) on Exelon Patch with a thin ball point pen.

Exelon Patch should be worn continuously until it is time to replace it with a new patch. Avoid placing the patch where it could be rubbed off by clothing.

How to remove Exelon Patch:

Gently pull at one edge of Exelon Patch to remove it completely from the skin.

How to dispose of Exelon Patch:

After the patch has been removed, fold it in half with the adhesive sides on the inside and press them together. Return the used patch to its original pouch and discard safely out of the reach and sight of children and pets as there may be medicine left over in the patch. Wash your hands with soap and water after removing the patch.

Can Exelon Patch be worn when bathing, swimming, or in the sun?

Bathing, swimming, or showering should not affect the patch. When swimming, you can wear the patch under your swimsuit. Make sure the patch does not loosen during these activities.

The patch should not be exposed to any external heat sources (excessive sunlight, saunas, solariums) for long periods of time.

What to do if Exelon Patch falls off:

If the patch falls off, a new patch should be applied for the rest of the day and then replaced the next day at the same time as usual.

When and how long to apply Exelon Patch:

To benefit from your medicine you must apply a new patch every day.

Tell your caregiver that you are applying Exelon Patch. Also tell your caregiver if you have not been applying Exelon Patch for several days.

What to do if you apply more Exelon p atch es than you should :

If you accidentally apply more Exelon patches than you should, remove all Exelon patches from your skin, and then inform your doctor that you have accidentally applied more Exelon patches than you should have. You may require medical attention. Some people who have accidentally taken too much Exelon have experienced nausea, vomiting, diarrhea, high blood pressure and hallucinations. Slow heartbeat and fainting may also occur.

If you forget to apply Exelon Patch:

If you have forgotten to apply Exelon Patch, apply a new patch immediately. You may apply the next patch at the usual time the next day. Do not apply two Exelon patches to make up for the one that you missed.

If you have not been applying Exelon Patch for several days do not apply the next patch before you have talked to your doctor.

Possible side effects :

Like all medicines, Exelon Patch can cause side effects, although not everybody gets them.

Do not be alarmed by this list of possible side effects. You may not experience any of them.

You may tend to see side effects more frequently when you start your medication or increase to a higher dose. In most cases, side effects will gradually disappear as your body becomes used to the medicine. Gastrointestinal reactions such as nausea (feeling sick) and vomiting (being sick) are the most common side effects. The other common side effects are: loss of appetite, anxiety, difficulty sleeping, dizziness, headache, diarrhea, stomach discomfort after meals, stomach pain, skin reactions at the application site (redness, itching, irritation, swelling), fatigue, weakness, and weight loss.

Some side effects could become serious:

Common: depression.

Uncommon: severe confusion, hallucinations, vascular accident involving the brain (loss of coordination, difficulty in speaking or breathing and signs of brain disorder), fainting, problems with heart rhythm (irregular or fast or slow heartbeat), gastric ulcer and gastrointestinal hemorrhage (blood in stools or when vomiting).

If you experience any of these, remove Exelon Patch and tell your doctor right away.

Other side effects:

Uncommon: agitation, drowsiness, sweating and a general feeling of being unwell.

If any of these affect you severely, tell your doctor.

Additional side effects have been reported with Exelon capsules or oral solution:

Common: confusion and trembling.

Uncommon: changes in liver function tests and accidental falls.

Rare: convulsions, chest pain, duodenal ulcer and rash.

Very rare: urinary tract infection, high blood pressure, inflammation of the pancreas (severe upper stomach pain, often with nausea and vomiting) and severe vomiting that can lead to a rupture of the esophagus.

In addition, you should contact your doctor or pharmacist if you experience any other possible side effects not mentioned in this leaflet.

How to store Exelon Patch :

Do not use Exelon Patch after the expiration date shown on the carton and pouch.

Store at room temperature, 59-86°F (15-30°C).

Do not use any Exelon Patch that is damaged or shows signs of tampering.

Keep Exelon Patch out of the reach and sight of children and pets.

Distributed by:

Novartis Pharmaceuticals Corporation

East Hanover, New Jersey 07936

Repackaged by:

Rebel Distributors Corp

Thousand Oaks, CA 91320

PRINCIPAL DISPLAY PANEL

Package Label – 4.6 mg / 24 hours

Rx Only

EXELON® Patch

(rivastigmine transdermal system)

Each System Delivers 4.6 mg/24 hours